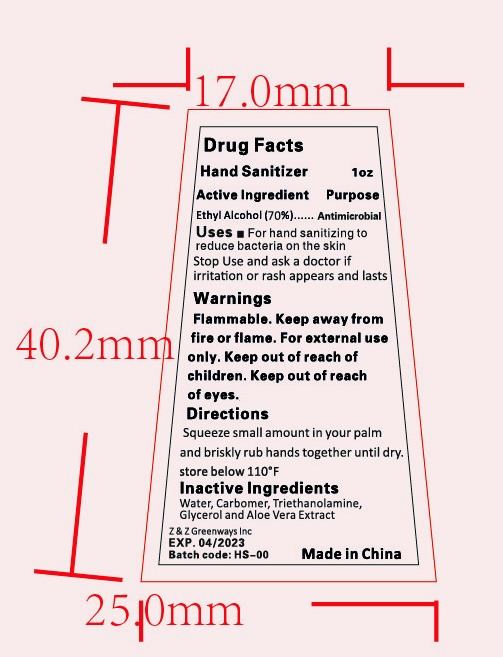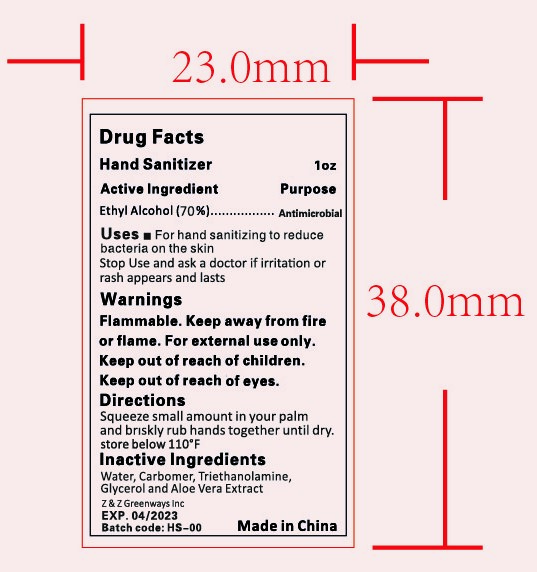 DRUG LABEL: HAND SANITIZER
NDC: 47993-228 | Form: GEL
Manufacturer: NINGBO JIANGBEI OCEAN STAR TRADING CO.,LTD
Category: otc | Type: HUMAN OTC DRUG LABEL
Date: 20201104

ACTIVE INGREDIENTS: ALCOHOL 70 g/112 mL
INACTIVE INGREDIENTS: TRIETHANOLAMINE BENZOATE 3 g/112 mL; GLYCERIN 2 g/112 mL; CARBOMER 940 12 g/112 mL; ALOE VERA LEAF 1 g/112 mL; WATER 12 g/112 mL

47993-228

Active ingredients

Ethyl Alcohol 70%

PURPOSE

Antiseptic

Warnings:

Flammable. Keep away from fire or flame. For external use only. Keep out of reach of children. Keep out of reach of eyes.

Uses：

For hand sanitizing to readuce bacteria on the skin.

Stop use and ask a doctor if irritation or rash appears and lasts.

Stop use and ask a doctor if irritation or rash appears and lasts.

Directions:

Squeeze small amounnt in your palm and briskly rub hands together until dry.

OTHER SAFETY INFORMATION

Store below 110℉

Keep out of reach of children.

Inactive Ingredients:

Water,Carbomer ,Triethanolamine,Glycerin and Aloe Vera Extract